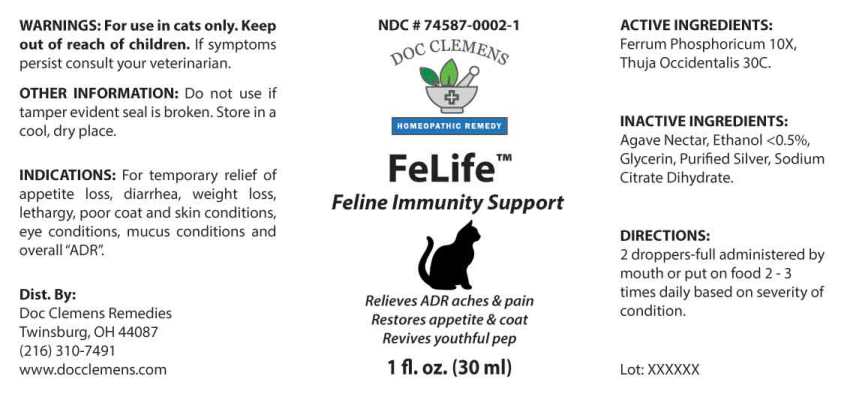 DRUG LABEL: Felife
NDC: 74587-0002 | Form: LIQUID
Manufacturer: Feel Good Pets LLC
Category: homeopathic | Type: OTC ANIMAL DRUG LABEL
Date: 20210419

ACTIVE INGREDIENTS: FERROSOFERRIC PHOSPHATE 10 [hp_X]/1 mL; THUJA OCCIDENTALIS LEAFY TWIG 30 [hp_C]/1 mL
INACTIVE INGREDIENTS: GLYCERIN; SILVER; TRISODIUM CITRATE DIHYDRATE; AGAVE TEQUILANA JUICE; ALCOHOL

DRUG FACTS:

ACTIVE INGREDIENTS:

Ferrum Phosphoricum 10X, Thuja Occidentalis 30C.

INDICATIONS:

For temporary relief of appetite loss, diarrhea, weight loss, lethargy, poor coat and skin conditions, eye conditions, mucus conditions and overall "ADR".

WARNINGS:

For use in cats only. Keep out of reach of childern. If symptoms persist consult your veterinarian.

KEEP OUT OF THE REACH OF CHILDREN:

Keep out of reach of children.

DIRECTIONS:

2 droppers-full administered by mouth or put on food 2-3 times daily based on severity of condition.

INDICATIONS:

For temporary relief of appetite loss, diarrhea, weight loss, lethargy, poor coat and skin conditions, eye conditions, mucus conditions and overall "ADR".

INACTIVE INGREDIENTS:

Agave Nectar, Ethanol <0.5%, Glycerin, Purified Silver, Sodium Citrate Dihydrate.

QUESTIONS:

Dist. BY:

Doc Clemens Remedies

Twinsburg, OH 44087

(216) 310-7491

www.docclemens.com

PACKAGE LABEL DISPLAY:

NDC # 74587-0002-1

DOC CLEMENS

HOMEOPATHIC REMEDY

FeLife

Feline Immunity Support

1 fl. oz. (30 ml)